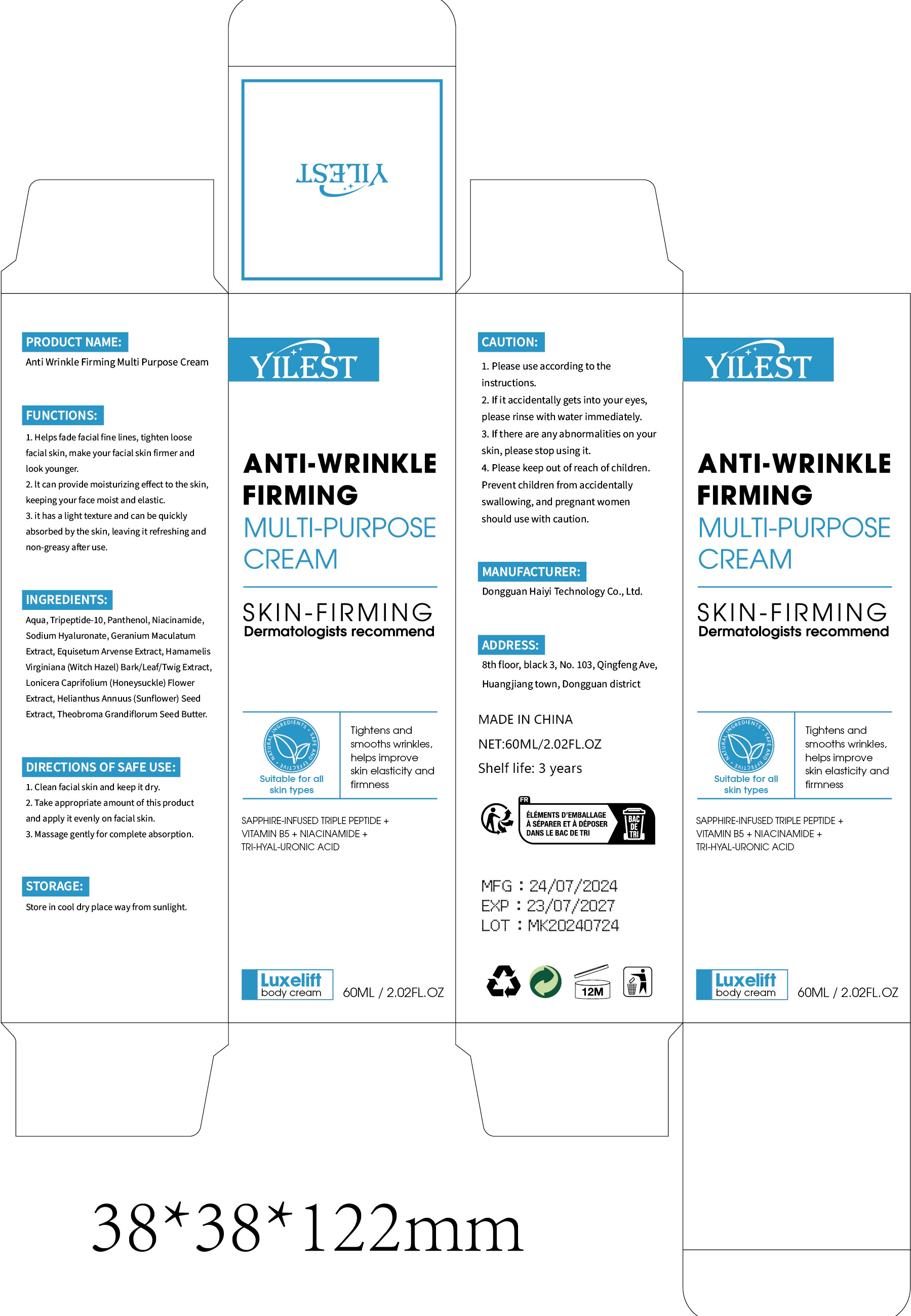 DRUG LABEL: Anti Wrinkle Firming Multi Purpose Cream
NDC: 84732-035 | Form: CREAM
Manufacturer: Dongguan Haiyi Technology Co.,Ltd.
Category: otc | Type: HUMAN OTC DRUG LABEL
Date: 20241009

ACTIVE INGREDIENTS: THEOBROMA GRANDIFLORUM SEED BUTTER 1 mg/100 mL
INACTIVE INGREDIENTS: PANTHENOL; NIACINAMIDE; PEG-9 DIGLYCIDYL ETHER/SODIUM HYALURONATE CROSSPOLYMER; TRIPEPTIDE-10 CITRULLINE; EQUISETUM ARVENSE BRANCH; HAMAMELIS VIRGINIANA TOP; LONICERA CAPRIFOLIUM FLOWER; WATER; GERANIUM MACULATUM ROOT; SUNFLOWER SEED

Active ingredient

Theobroma Grandiflorum Seed Butter

Inactive ingredient

Aqua,Tripeptide-10, Panthenol, Niacinamide.Sodium Hyaluronate, Geranium Maculatum Extract, Equisetum Arvense Extract, Hamamelis Virginiana (Witch Hazel) Bark/Leaf/Twig Extract,Lonicera Caprifolium (Honeysuckle) Flower Extract, Helianthus Annuus (Sunflower) Seed Extract

Purpose section

1.Helps fade facial fine lines, tighten loosefacial skin, make your facial skin firmer and look younger.
2. lt can provide moisturizing effect to the skin,keeping your face moist and elastic.

3. it has a light texture and can be quicklyabsorbed by the skin, leaving it refreshing andnon-greasy after use.

Warning

1. Please use according to the instructions.
2. lf it accidentally gets into your eyes,please rinse with water immediately.

3. lf there are anyabnormalities on yourskin, please stop using it.
4. Please keep out of reach of children.Prevent children from accidentallyswallowing,and pregnant womenshould use with caution.

stop use

lf there are any abnormalities on your skin, please stop using it.

not use

Not suitable for use by children, pregnantor breast feeding people.

OUT OF CHILDREN

KEEP THE PRODUCT OUT OF REACH OF CHILDREN to

HOW TO USE

1. Clean facial skin and keep it dry.

2. Take appropriate amount of this productand apply it evenly on facial skin.

3. Massage gentlyfor complete absorption.

Dosage

Once a day in the morning and evening